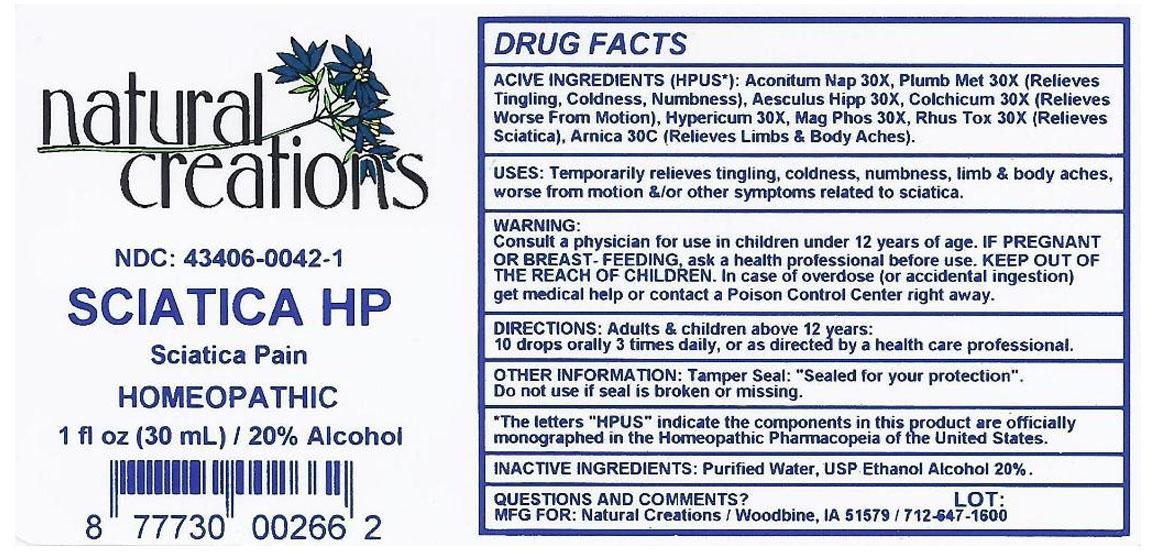 DRUG LABEL: SCIATICA HP
NDC: 43406-0042 | Form: LIQUID
Manufacturer: Natural Creations, Inc.
Category: homeopathic | Type: HUMAN OTC DRUG LABEL
Date: 20121114

ACTIVE INGREDIENTS: AESCULUS HIPPOCASTANUM FLOWER 30 [hp_X]/1 mL; ACONITUM NAPELLUS 30 [hp_X]/1 mL; COLCHICUM AUTUMNALE BULB 30 [hp_X]/1 mL; HYPERICUM PERFORATUM 30 [hp_X]/1 mL; MAGNESIUM PHOSPHATE, DIBASIC TRIHYDRATE 30 [hp_X]/1 mL; LEAD 30 [hp_X]/1 mL; TOXICODENDRON PUBESCENS LEAF 30 [hp_X]/1 mL; ARNICA MONTANA 30 [hp_C]/1 mL
INACTIVE INGREDIENTS: WATER; ALCOHOL

SCIATICA HP

ACTIVE INGREDIENT

ACTIVE INGREDIENTS (HPUS*): Aesculus hippocastanum 30X, Aconitum Napellus 30X, Colchicum Autumnale 30X, Hypericum Perforatum 30X, Magnesia Phosphorica 30X, Plumbum Metallicum 30X, Rhus Toxicodedron 30X, Arnica Montana 30C

INDICATIONS AND USAGE

USES: Temporarily relieves tingling, coldness, numbness, limb & body aches, worse from motion &/or other symptoms related to sciatica.

WARNING:

Consult a physician for use in children under 12 years of age. IF PREGNANT OR BREAST-FEEDING, ask a health care professional before use. KEEP OUT OF THE REACH OF CHILDREN. In case of overdose (or accidental ingestion) get medical help or contact a Poison Control Center right away.

DOSAGE AND ADMINISTRATION

DIRECTIONS: Adults and children above 12 years: 10 drops orally 3 times daily, or as directed by a health care professional.

OTHER INFORMATION: Tamper Seal: "Sealed for your protection."

Do not use if seal is broken or missing.

REFERENCES

*The letters "HPUS" indicate the components in the product are officially monographed in the Homeopathic Pharmacopeia of the United States.

INACTIVE INGREDIENTS: Purified Water, USP Ethanol Alcohol 20%

QUESTIONS AND COMMENTS?

MFG FOR: Natural Creations / Woodbine, IA / 51579 712.647.1600

LOT:

PURPOSE

USES: Temporarily relieves tingling, coldness, numbness, limb & body aches, worse from motion &/or other symptoms related to sciatica.

KEEP OUT OF REACH OF CHILDREN

KEEP OUT OF THE REACH OF CHILDREN. In case of overdose (or accidental ingestion) get medical help or contact a Poison Control Center.

PACKAGE LABEL

NDC: 43406-0042-1

SCIATICA HP

Sciatica Pain

HOMEOPATHIC

1 fl oz (30 mL) / 20% Alcohol

UPC: 877730002662